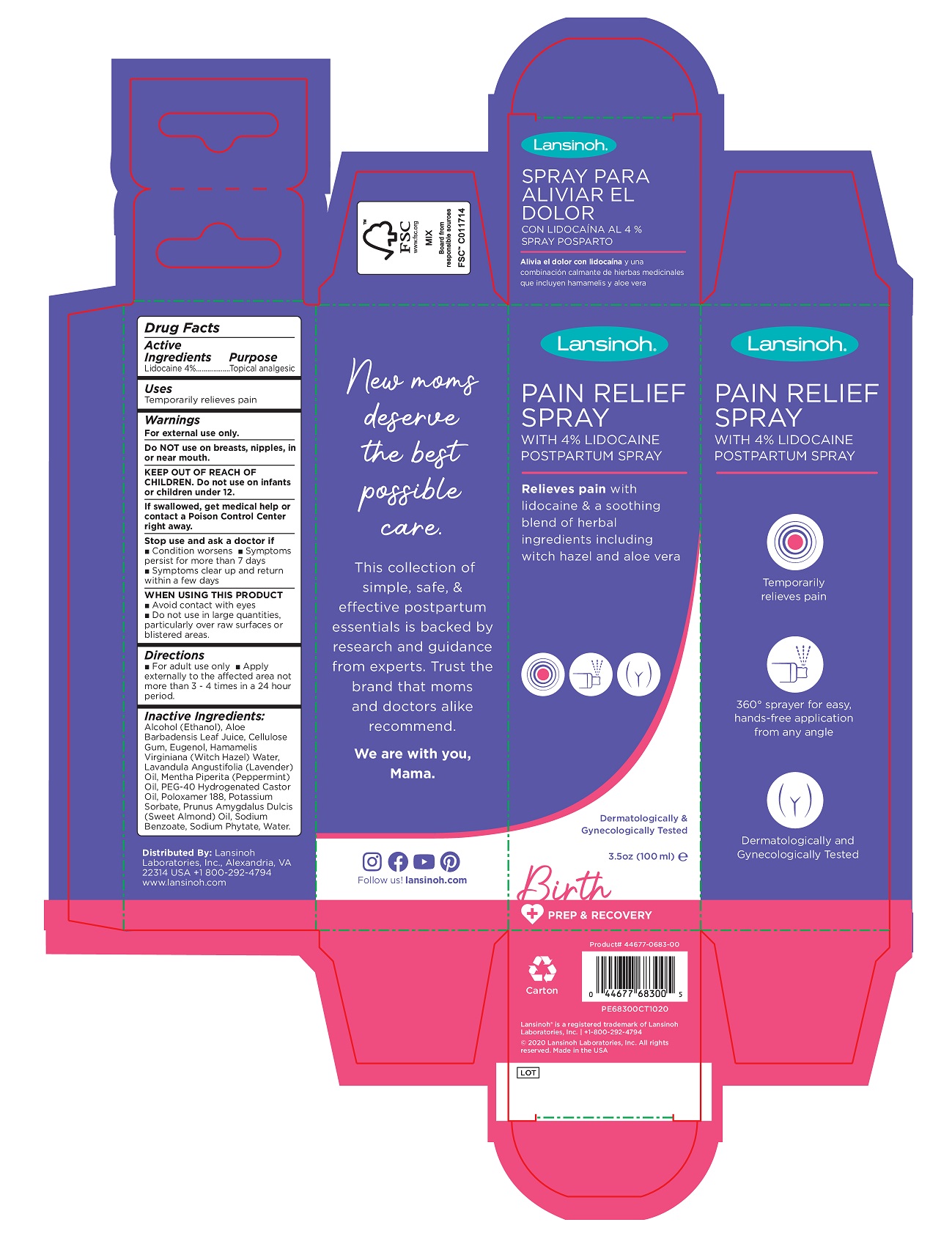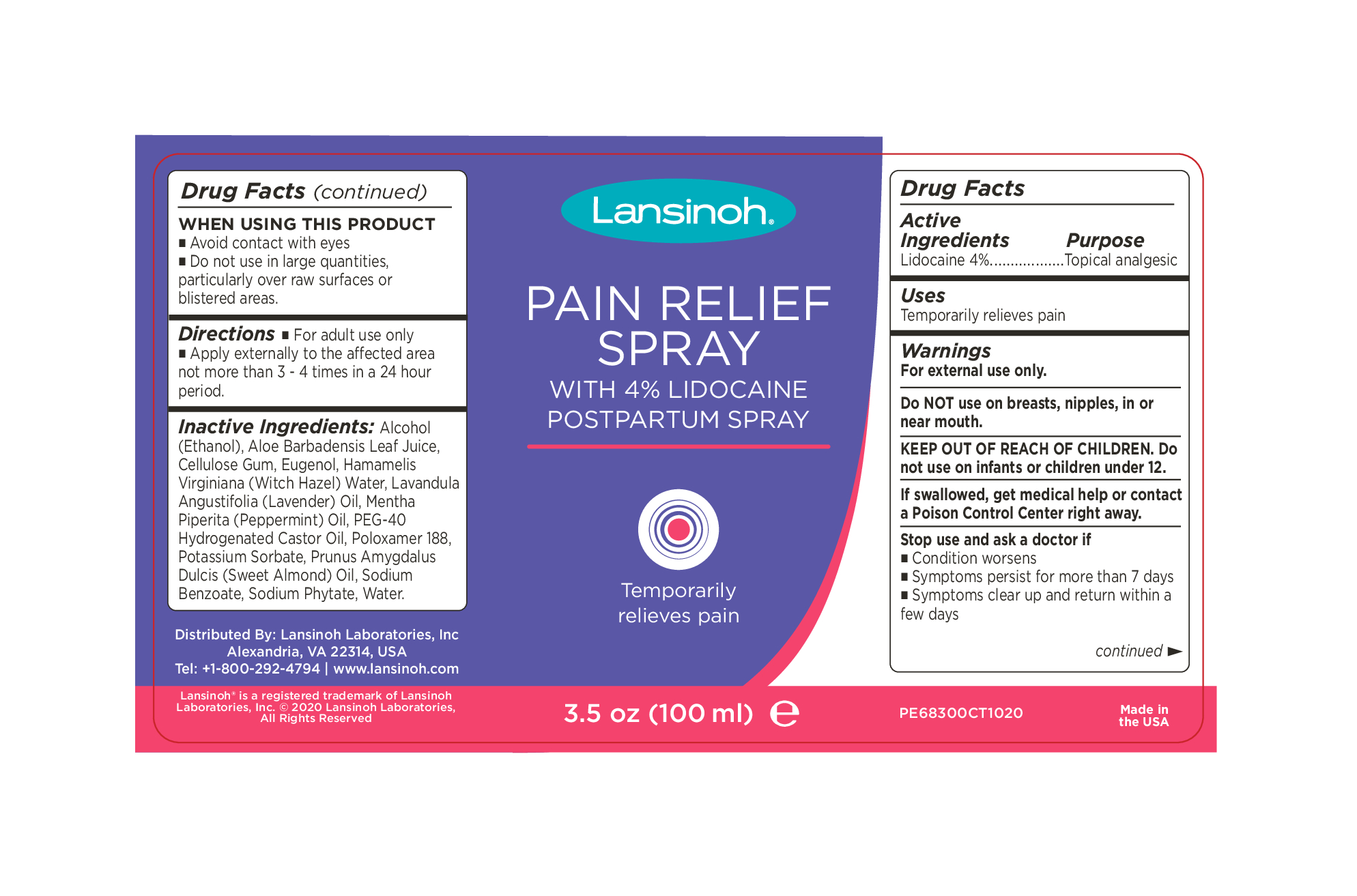 DRUG LABEL: Lansinoh Pain Relieving
NDC: 53997-001 | Form: SPRAY
Manufacturer: Lansinoh Laboratories Inc
Category: otc | Type: HUMAN OTC DRUG LABEL
Date: 20250905

ACTIVE INGREDIENTS: LIDOCAINE 4 g/100 mL
INACTIVE INGREDIENTS: ALOE VERA WHOLE; PEG-40 CASTOR OIL; EUGENOL; ALCOHOL; WITCH HAZEL; WATER; SODIUM BENZOATE; POLOXAMER 188; POTASSIUM SORBATE; ALMOND OIL; PEPPERMINT OIL; CARBOXYMETHYLCELLULOSE SODIUM (0.7 CARBOXYMETHYL SUBSTITUTION PER SACCHARIDE; 2300 MPA.S AT 1%); LAVENDER OIL; PHYTATE SODIUM

Lansinoh Pain Relieving Spray

DRUG FACTS

Active Ingredient | Purpose
Lidocaine 4% | Topical Analgesic

Stop use and ask a doctor if
■ Condition worsens
■ Symptoms persist for more than 7 days
■ Symptoms clear up and return within a
few day

KEEP OUT OF REACH OF CHILDREN. Do
not use on infants or children under 12.

WARNINGS

For external use only.
Do NOT use on breasts, nipples, in or
near mouth.
KEEP OUT OF REACH OF CHILDREN. Do
not use on infants or children under 12.
If swallowed, get medical help or contact
a Poison Control Center right away.

Stop use and ask a doctor if
■ Condition worsens
■ Symptoms persist for more than 7 days
■ Symptoms clear up and return within a
few days

DOSAGE AND ADMINISTRATION

Directions ■ For adult use only
■ Apply externally to the affected area not more than 3 - 4 times in a 24 hour period.

Inactive Ingredients:

Alcohol (Ethanol), Aloe Barbadensis Leaf Juice, Cellulose Gum, Eugenol, Hamamelis Virginiana (Witch Hazel) Water, Lavandula Angustifolia (Lavender) Oil, Mentha Piperita (Peppermint) Oil, PEG-40 Hydrogenated Castor Oil, Poloxamer 188, Potassium Sorbate, Prunus Amygdalus Dulcis (Sweet Almond) Oil, Sodium Benzoate, Sodium Phytate, Water.

Distributed By: Lansinoh Laboratories, Inc
Alexandria, VA 22314, USA
Tel: +1-800-292-4794 | www.lansinoh.com

WARNINGS

FOR EXTERNAL USE ONLY

INDICATIONS AND USAGE

For external use only

PURPOSE

Topical Analgesic